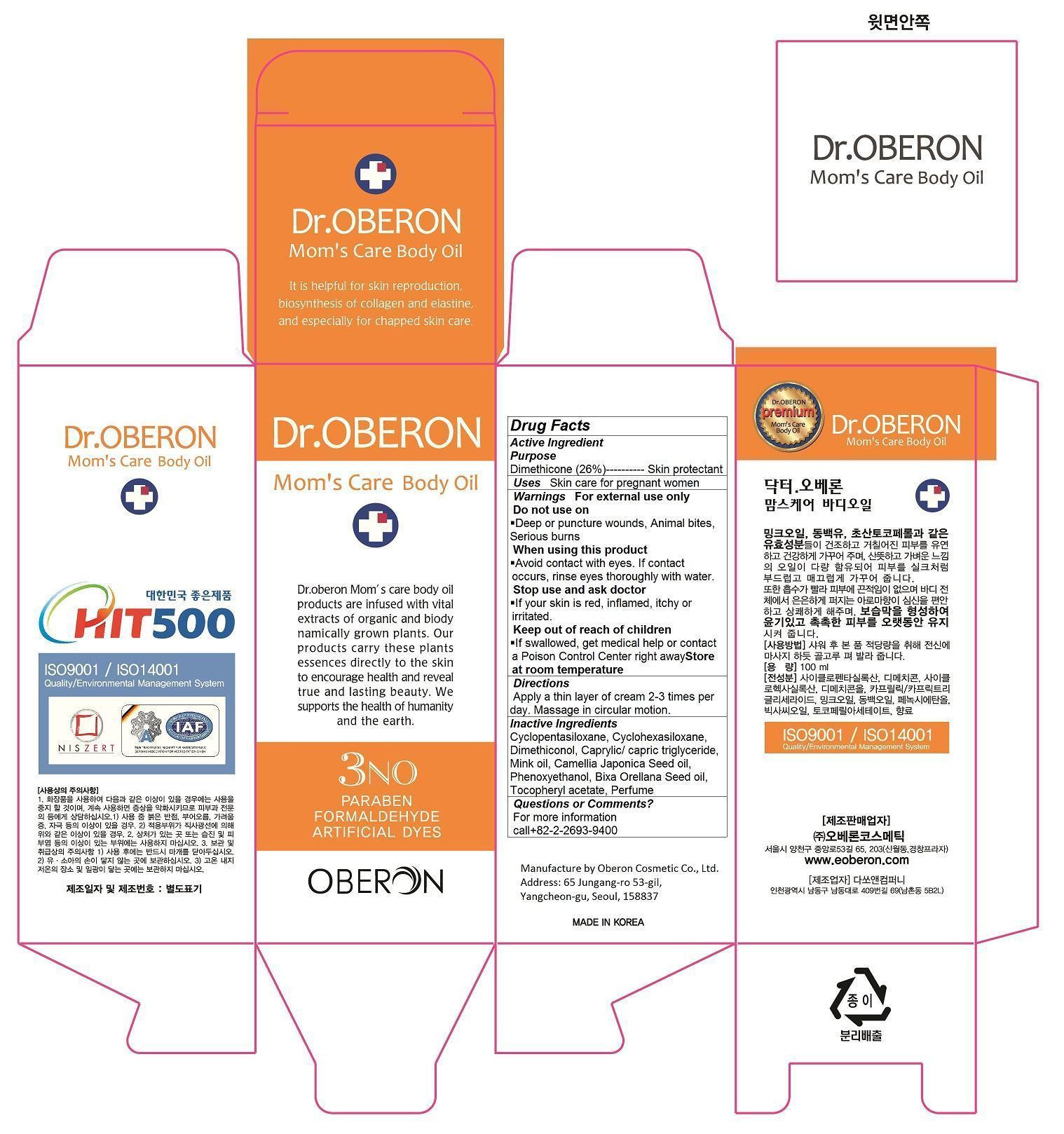 DRUG LABEL: Dr. OBERON MOMS CARE BODY OIL
NDC: 52891-102 | Form: OIL
Manufacturer: Oberon Cosmetic Co., Ltd.
Category: otc | Type: HUMAN OTC DRUG LABEL
Date: 20140612

ACTIVE INGREDIENTS: DIMETHICONE 26 1/100 mL
INACTIVE INGREDIENTS: CYCLOMETHICONE 5; CYCLOMETHICONE 6; DIMETHICONOL (40 CST); TRICAPRIN; CAMELLIA JAPONICA SEED OIL; PHENOXYETHANOL; BIXA ORELLANA SEED OIL; .ALPHA.-TOCOPHEROL ACETATE

Dr. OBERON MOM'S CARE BODY OIL